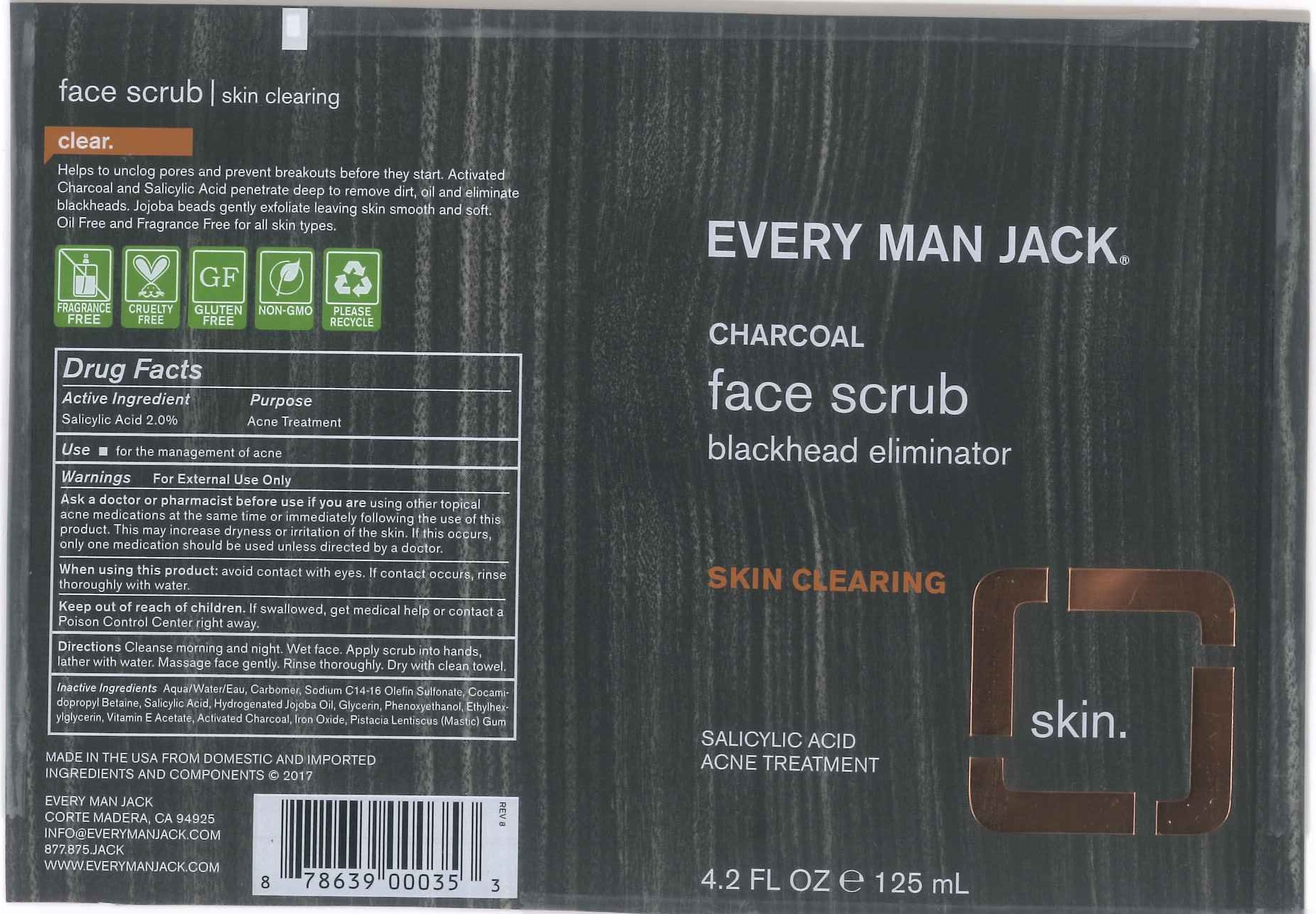 DRUG LABEL: EVERY MAN JACK CHARCOAL FACE SCRUB
NDC: 57934-5012 | Form: CREAM
Manufacturer: EVERY MAN JACK
Category: otc | Type: HUMAN OTC DRUG LABEL
Date: 20211217

ACTIVE INGREDIENTS: SALICYLIC ACID 2 g/100 mL
INACTIVE INGREDIENTS: WATER; CARBOMER HOMOPOLYMER TYPE C (ALLYL PENTAERYTHRITOL CROSSLINKED); SODIUM C14-16 OLEFIN SULFONATE; COCAMIDOPROPYL BETAINE; HYDROGENATED JOJOBA OIL; GLYCERIN; PHENOXYETHANOL; ETHYLHEXYLGLYCERIN; .ALPHA.-TOCOPHEROL ACETATE; ACTIVATED CHARCOAL; FERROSOFERRIC OXIDE; PISTACIA LENTISCUS RESIN

EVERY MAN JACK - CHARCOAL FACE SCRUB - 57934-5012

ACTIVE INGREDIENT

SALICYLIC ACID 2%

PURPOSE

ACNE TREATMENT

USE

- FOR THE MANAGEMENT OF ACNE

WARNINGS

FOR EXTERNAL USE ONLY.

ASK A DOCTOR OR PHARMACIST BEFORE USE IF YOU ARE USING OTHER TOPICAL ACNE MEDICATIONS AT THE SAME TIME OR IMMEDIATELY FOLLOWING THE USE OF THIS PRODUCT. THIS MAY INCREASE DRYNESS OR IRRITATION OF THE SKIN. IF THIS OCCURS, ONLY ONE MEDICATION SHOULD BE USED UNLESS DIRECTED BY A DOCTOR.

WHEN USING THIS PRODUCT: AVOID CONTACT WITH EYES. IF CONTACT OCCURS, RINSE THOROUGHLY WITH WATER.

KEEP OUT OF REACH OF CHILDREN. IF SWALLOWED, GET MEDICAL HELP OR CONTACT A POISON CONTROL CENTER RIGHT AWAY.

DIRECTIONS

CLEANSE MORNING AND NIGHT. WET FACE. APPLY SCRUB INTO HANDS, LATHER WITH WATER. MASSAGE FACE GENTLY. RINSE THOROUGHLY. DRY WITH CLEAN TOWEL.

INACTIVE INGREDIENTS

AQUA/WATER/EAU, CARBOMER, SODIUM C14-16 OLEFIN SULFONATE, COCAMIDOPROPYL BETAINR, SALICYLIC ACID, HYDROGENATED JOJOBA OIL, GLYCERIN, PHENOXYETHANOL, ETHYLHEXYLGLYCERIN, VITAMIN E ACETATE, ACTIVATED CHARCOAL, IRON OXIDE, PISTACIA LENTISCUS (MASTIC) GUM